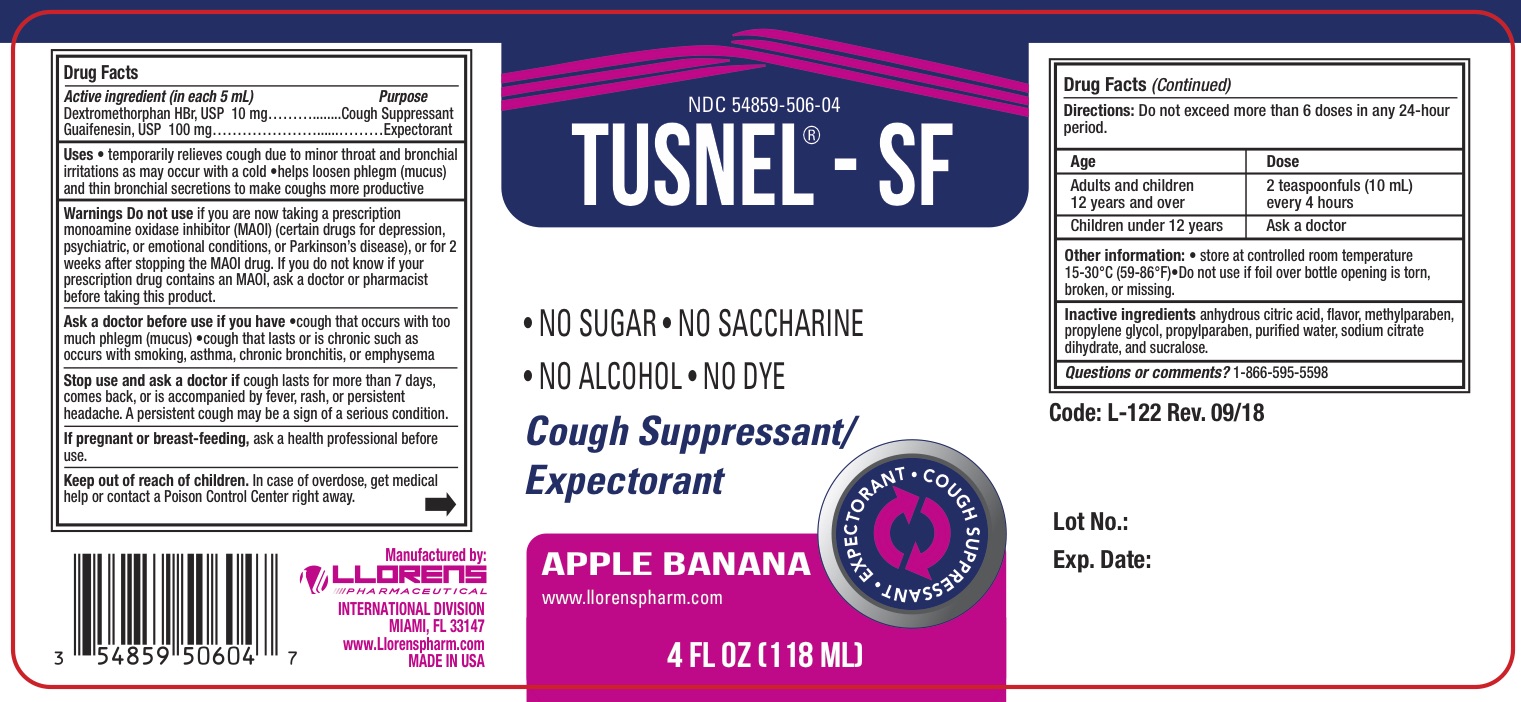 DRUG LABEL: Tusnel
NDC: 54859-506 | Form: LIQUID
Manufacturer: Llorens Pharmaceutical International Division, Inc.
Category: otc | Type: HUMAN OTC DRUG LABEL
Date: 20251231

ACTIVE INGREDIENTS: DEXTROMETHORPHAN HYDROBROMIDE 10 mg/5 mL; GUAIFENESIN 100 mg/5 mL
INACTIVE INGREDIENTS: ANHYDROUS CITRIC ACID; METHYLPARABEN; PROPYLENE GLYCOL; PROPYLPARABEN; WATER; TRISODIUM CITRATE DIHYDRATE; SUCRALOSE

Llorens-Tusnel SF 506

ACTIVE INGREDIENT

In each 5 mL

Dextromethorphan HBr - 10 mg

Guaifenesin - 100 mg

PURPOSE

Cough Suppressant

Expectorant

Uses

- temporarily relieves cough due to minor throat and bronchial irritation as may occur with a cold
- helps loosen phlegm (mucus) and thin bronchial secretions to make coughs more productive

Warnings

Do not useif you are now taking a prescription monoamine oxidase inhibitor (MAOI) (certain drugs for depression, psychiatric, or emotional conditions, or Parkinson’s disease), or for 2 weeks after stopping the MAOI drug. If you do not know if your prescription drug contains an MAOI, ask a doctor or pharmacist before taking this product.

Ask a doctor before us if you have

- cough that occurs with too much phlegm (mucus)
- cough that lasts or is chronic such as occurs with smoking, asthma, chronic bronchitis, or emphysema

Stop use and ask a doctor if cough lasts for more than 7 days, comes back, or is accompanied by fever, rash, or persistent headache. A persistent cough may be a sign of a serious condition.

PREGNANCY OR BREAST FEEDING

If pregnant or breast-feeding, ask a health professional before use.

Keep out of reach of children. In case of overdose, get medical help or contact a Poison Control Center right away.

DOSAGE AND ADMINISTRATION

Directions:Do not exceed more than 6 doses in any 24-hour period.

Age | Dose
Adults and children 12 years and over | 2 teaspoonfuls (10 mL) every 4 hours
Children under 12 years | Ask a doctor

INACTIVE INGREDIENT

Inactive ingredients anhydrous citric acid, avor, methylparaben, propylene glycol, propylparaben, puri ed water, sodium citrate dihydrate, and sucralose.

Questions or comments?1-866-595-5598